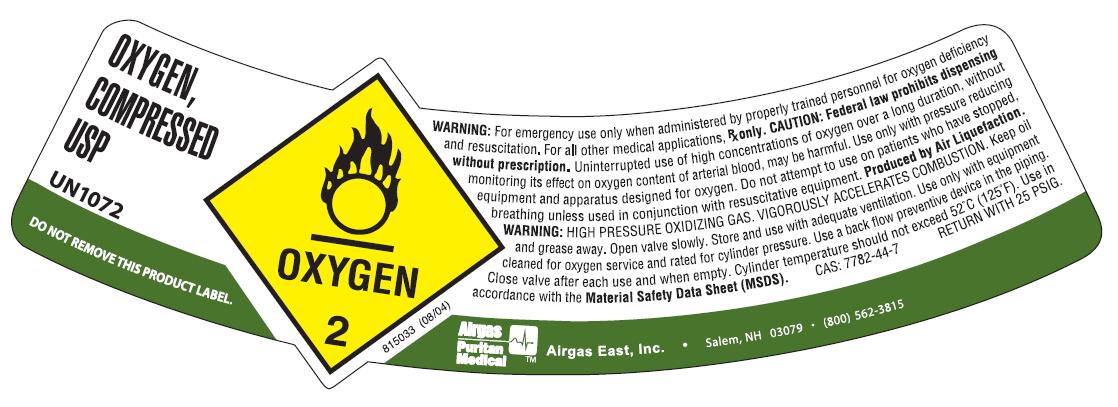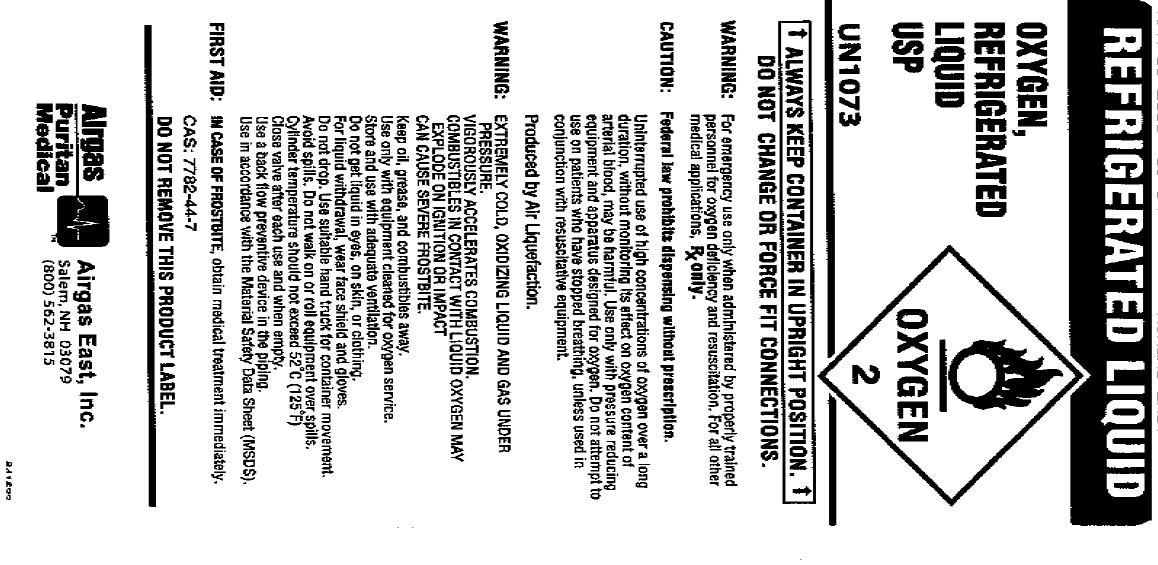 DRUG LABEL: Oxygen
NDC: 25543-001 | Form: GAS
Manufacturer: Airgas East, Inc.
Category: prescription | Type: HUMAN PRESCRIPTION DRUG LABEL
Date: 20110217

ACTIVE INGREDIENTS: Oxygen 995 mL/1 L

oxygen

PACKAGE LABEL

OXYGEN, COMPRESSED LIQUID USP UN1072 DO NOT REMOVE THIS PRODUCT LABEL. OXYGEN 2 815033 (08/04)
WARNING: For emergency use only when administered by properly trained personnel for oxygen deficiency and resuscitation. For all other medical applications, Rx only.
CAUTION: Federal law prohibits dispensing without prescription. Uninterrupted use of high concentrations of oxygen over a long duration, without monitoring its effect on oxygen content of arterial blood, may be harmful. Use only with pressure reducing equipment and apparatus designed for oxygen. Do not attempt to use on patients who have stopped breathing, unless used in conjunction with resuscitative equipment. Produced by Air Liquefaction.
WARNING: HIGH PRESSURE OXIDIZING GAS. VIGOROUSLY ACCELERATES COMBUSTION. Keep oil, grease away. Open valve slowly. Store and use with adequate ventilation. Use only with equipment cleaned for oxygen service and rated for cylinder pressure. Use back flow preventive device in the piping. Close valve after each use and when empty. Cylinder temperature should not exceed 52C (125F). Use in accordance with the Material Safety Data Sheets (MSDS). CAS: 7782-44-7 RETURN WITH 25 PSIG.
AIRGAS PURITAN MEDICAL AIRGAS EAST, Inc. Salem, NH 03079 (800) 562-3815

PACKAGE LABEL

REFRIGERATED LIQUID
OXYGEN, REFRIGERATED LIQUID USP UN1073 OXYGEN 2
ALWAYS KEEP CONTAINER IN UPRIGHT POSITION DO NOT CHANGE OR FORCEFIT CONNECTIONS
WARNING: For emergency use only when administered by properly trained personnel for oxygen deficiency and resuscitation. For all other medical applications, Rx only.
CAUTION: Federal law prohibits dispensing without prescription. Uninterrupted use of high concentrations of oxygen over a long duration, without monitoring its effect on oxygen content of arterial blood, may be harmful. Use only with pressure reducing equipment and apparatus designed for oxygen. Do not attempt to use on patients who have stopped breathing, unless used in conjunction with resuscitative equipment. Produced by Air Liquefaction.
WARNING: EXTREMELY COLD, OXIDIZING LIQUID AND GAS UNDER PRESSURE. VIGOROUSLY ACCELERATES COMBUSTION. COMBUSTIBLES IN CONTACT WITH LIQUID OXYGEN MAY EXPLODE ON IGNITION OR IMPACT. CAN CAUSE SEVERE FROSTBITE. Keep oil, grease and combustibles away. Use only with equipment cleaned for oxygen service. Store and use with adequate ventilation. Do not get liquid in eyes, on skin, or clothing. For liquid withdrawal, wear face shield and gloves. Do not drop. Use suitable hand truck for container movement. Avoid spills. Do not walk on or roll equipment over spills. Cylinder temperature should not exceed 52C (125F). Close valve after each use and when empty. Use back flow preventive device in the piping. Use in accordance with the Material Safety Data Sheets (MSDS).
FIRST AID: IN CASE OF FROSTBITE, obtain medical treatment immediately. CAS: 7782-44-7
DO NOT REMOVE THIS PRODUCT LABEL.
AIRGAS PURITAN MEDICAL AIRGAS EAST, Inc. Salem, NH 03079 (800) 562-3815